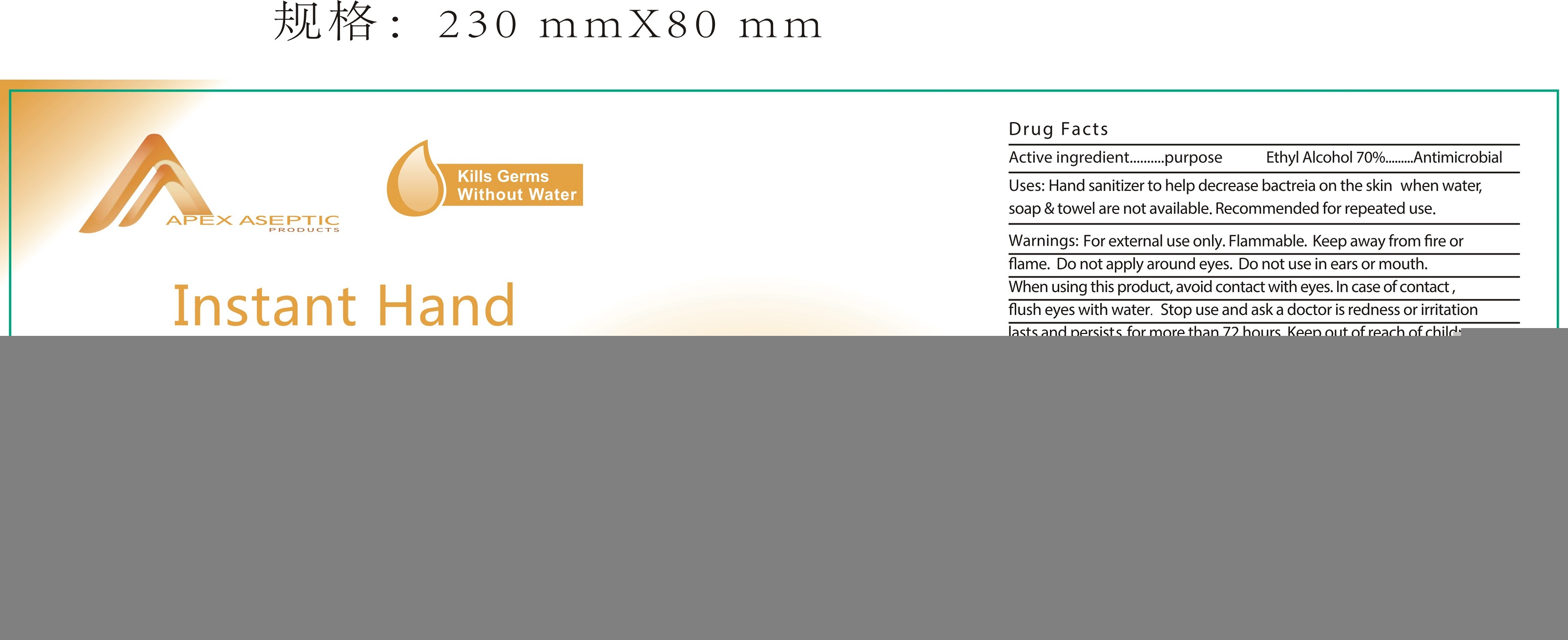 DRUG LABEL: APEX ASEPTIC Instant Hand Sanitizer with Aloe
NDC: 74614-008 | Form: SOLUTION
Manufacturer: TAIZHOU BENGTE FURNITURE CO.,LTD
Category: otc | Type: HUMAN OTC DRUG LABEL
Date: 20200414

ACTIVE INGREDIENTS: ALCOHOL 70 mL/100 mL
INACTIVE INGREDIENTS: WATER; TROLAMINE; GLYCERIN; PROPYLENE GLYCOL; SODIUM HYDROXIDE

Active ingredient

Ethyl Alcohol 70%

Purpose

Antimicrobial

Use

Hand sanitizer to help decrease bacteria on the skin. When water, soap and towel are not available. Recommended for repeated use.

KEEP OUT OF REACH OF CHILDREN

Children must be supervised in use of this product.

warnings:

Flamable, keep away from fire and flame.

For external use only

Do not apply around eyes. Do not use in ears, mouth.

When using this product, avoid contact with eyes. In case of contact, flush eyes with water.

Stop use and ask a doctor if redness or irritation lasts and persists for more than 72 hours

DOSAGE AND ADMINISTRATION

Pump as needed into your palms and spread on both hands. Rub into skin until dry.

Other Information: Store below 110℉ （43℃）.

Inactive ingredients

Water, Aloe, Glycerin, Carbomer, Tocopheryl Acetate, Triethanolamine.